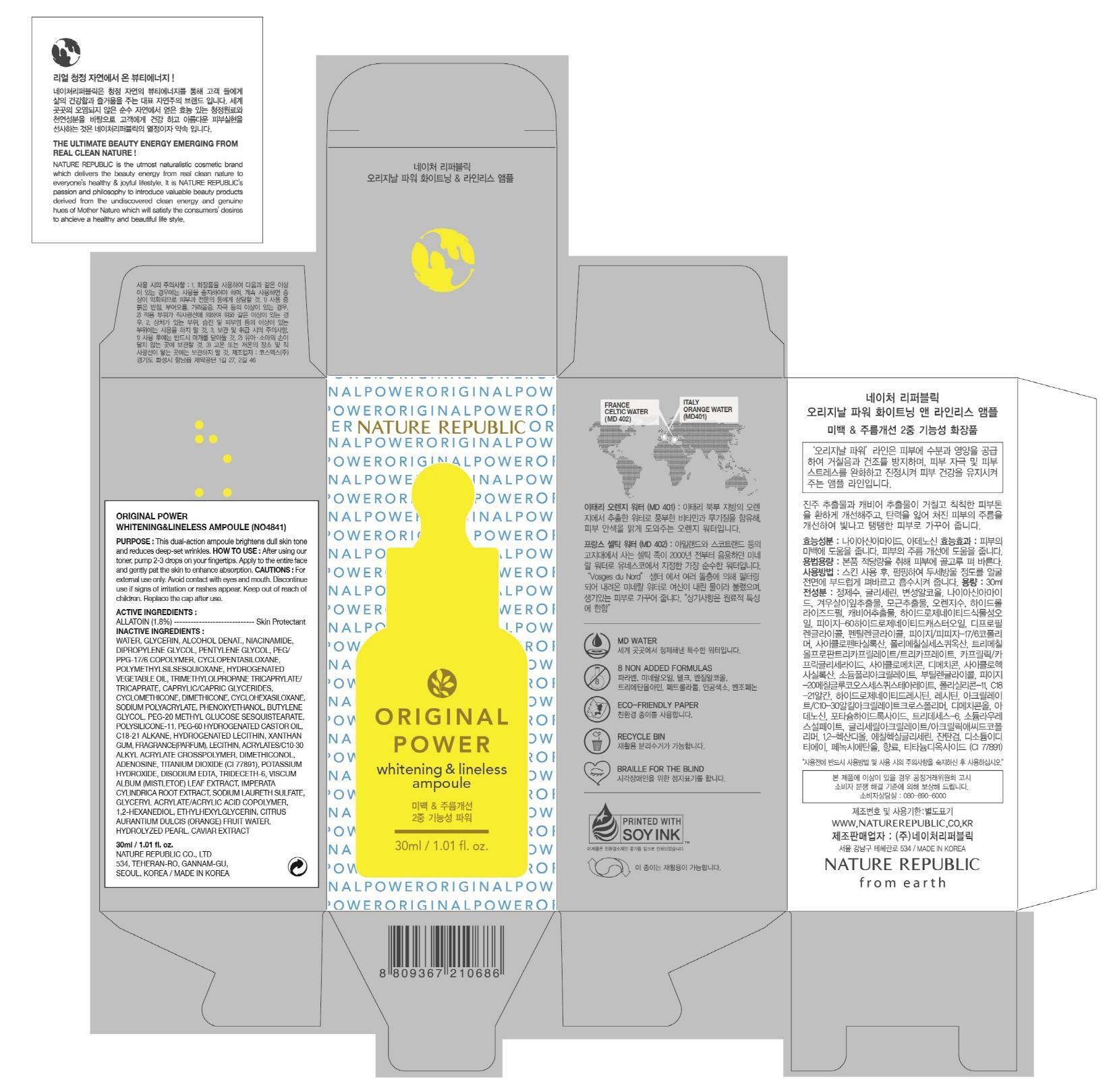 DRUG LABEL: ORIGINAL POWER WHITENING AND LINELESS AMPOULE
NDC: 51346-219 | Form: LIQUID
Manufacturer: NATURE REPUBLIC CO., LTD.
Category: otc | Type: HUMAN OTC DRUG LABEL
Date: 20130530

ACTIVE INGREDIENTS: ALLANTOIN 0.54 mg/30 mL
INACTIVE INGREDIENTS: Water; Glycerin

ACTIVE INGREDIENT

Active Ingredients: ALLANTOIN 1.8%

INACTIVE INGREDIENT

Inactive Ingredients:
Water, Glycerin, Alcohol Denat., Niacinamide, Dipropylene Glycol, Pentylene Glycol, PEG/PPG-17/6 Copolymer, Cyclopentasiloxane, Polymethylsilsesquioxane, Hydrogenated Vegetable Oil, Trimethylolpropane Tricaprylate/Tricaprate, Caprylic/Capric Glycerides,
Cyclomethicone, Dimethicone, Cyclohexasiloxane, Sodium Polyacrylate, Phenoxyethanol, Butylene Glycol, PEG-20 Methyl Glucose Sesquistearate, Polysilicone-11, PEG-60 Hydrogenated Castor Oil, C18-21 Alkane, Hydrogenated Lecithin, Xanthan Gum, Fragrance(Parfum), Lecithin, Acrylates/C10-30 Alkyl Acrylate Crosspolymer, Dimethiconol, Adenosine, Titanium Dioxide (CI 77891), Potassium Hydroxide, Disodium EDTA, Trideceth-6, Viscum Album (Mistletoe) Leaf Extract, Imperata Cylindrica Root Extract, Sodium Laureth Sulfate, Glyceryl Acrylate/Acrylic Acid Copolymer, 1,2-Hexanediol, Ethylhexylglycerin, Citrus Aurantium Dulcis (Orange) Fruit Water, Hydrolyzed Pearl, Caviar Extract

PURPOSE

Purpose: Skin Protectant

WARNINGS

Cautions:
For external use only.
Avoid contact with eyes and mouth.
Discontinue use if signs of irritation or rashes appear.
Keep out of reach of children.
Replace the cap after use.

KEEP OUT OF REACH OF CHILDREN

INDICATIONS AND USAGE

How to Use:
After using our toner, pump 2-3 drops on your fingertips.
Apply to the entire face and gently pat the skin to enhance absorption.

DOSAGE AND ADMINISTRATION

How to Use:
After using our toner, pump 2-3 drops on your fingertips.
Apply to the entire face and gently pat the skin to enhance absorption.